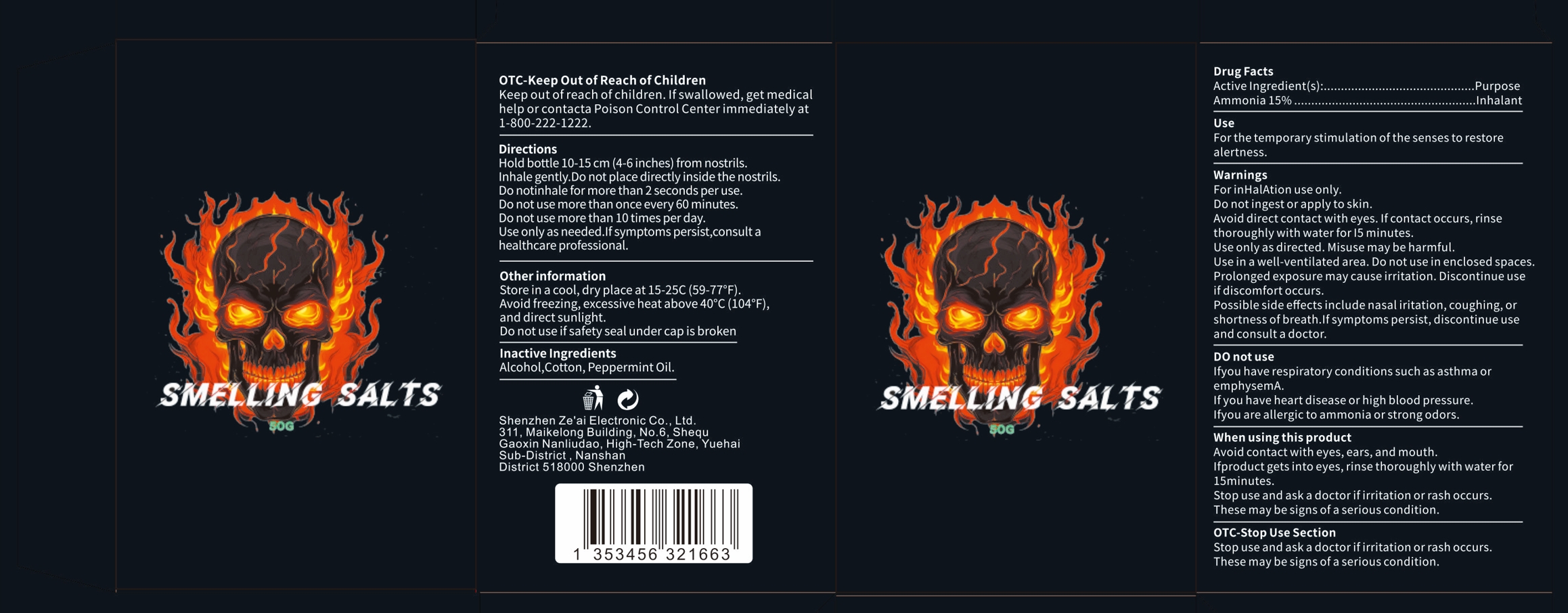 DRUG LABEL: smelling salts
NDC: 85765-003 | Form: INHALANT
Manufacturer: Shenzhen Ze'ai Electronic Co., Ltd.
Category: otc | Type: HUMAN OTC DRUG LABEL
Date: 20250910

ACTIVE INGREDIENTS: AMMONIA 0.15 g/1 g
INACTIVE INGREDIENTS: ALCOHOL; COTTON; PEPPERMINT OIL

85765-003 smelling salts

ACTIVE INGREDIENT

Ammonia 15%

PURPOSE

Inhalant

INDICATIONS AND USAGE

Forthe temporarystimulation of the senses to restore alertness

WARNINGS

ForinHalAtion use only.
Do notingest or apply to skin.
Avoid direct contact with eyes. lfcontact occurs, rinse thoroughly with water for l5 minutes.
Use only as directed. Misuse may be harmful.
Use in a well-ventilated area. Donot usein enclosed spaces.
Prolonged exposure may cause irritation. Discontinue use if discomfort occurs.
Possible side effectsinclude nasaliritation, coughing, or shortness of breath.lf symptoms persist, discontinue use and consult a doctor.

DO NOT USE

lf you have respiratory conditions such as asthma oremphysemA.
lf you have heart disease or high blood pressure.
lf you are allergic to ammonia or strongodors.

WHEN USING

Avoid contact with eyes,ears, and mouth.
lf product gets into eyes, rinse thoroughly with water for 15minutes.
Stop use and ask a doctor ifirritation or rash occurs.
These may be signs of a serious condition.

Stop use and ask a doctorifirritation orrash occursThese may be signs of a serious condition,

Keep out ofreach ofchildren.lfswallowed, get medical
help or contacta Poison Control Centerimmediately at 1-800-222-1222

DOSAGE AND ADMINISTRATION

Hold bottle 10-15 cm (4-6 inches) from nostrils.
Inhale gently.Do not place directlyinside the nostrils.
Do notinhale for more than 2 seconds per use.
Do not use more than once every 60 minutes.
Do not use more than 10 times per day.
Use only as needed.lfsymptoms persist,consult a healthcare professional.

INACTIVE INGREDIENT

Alcohol
Cotton
Peppermint Oil